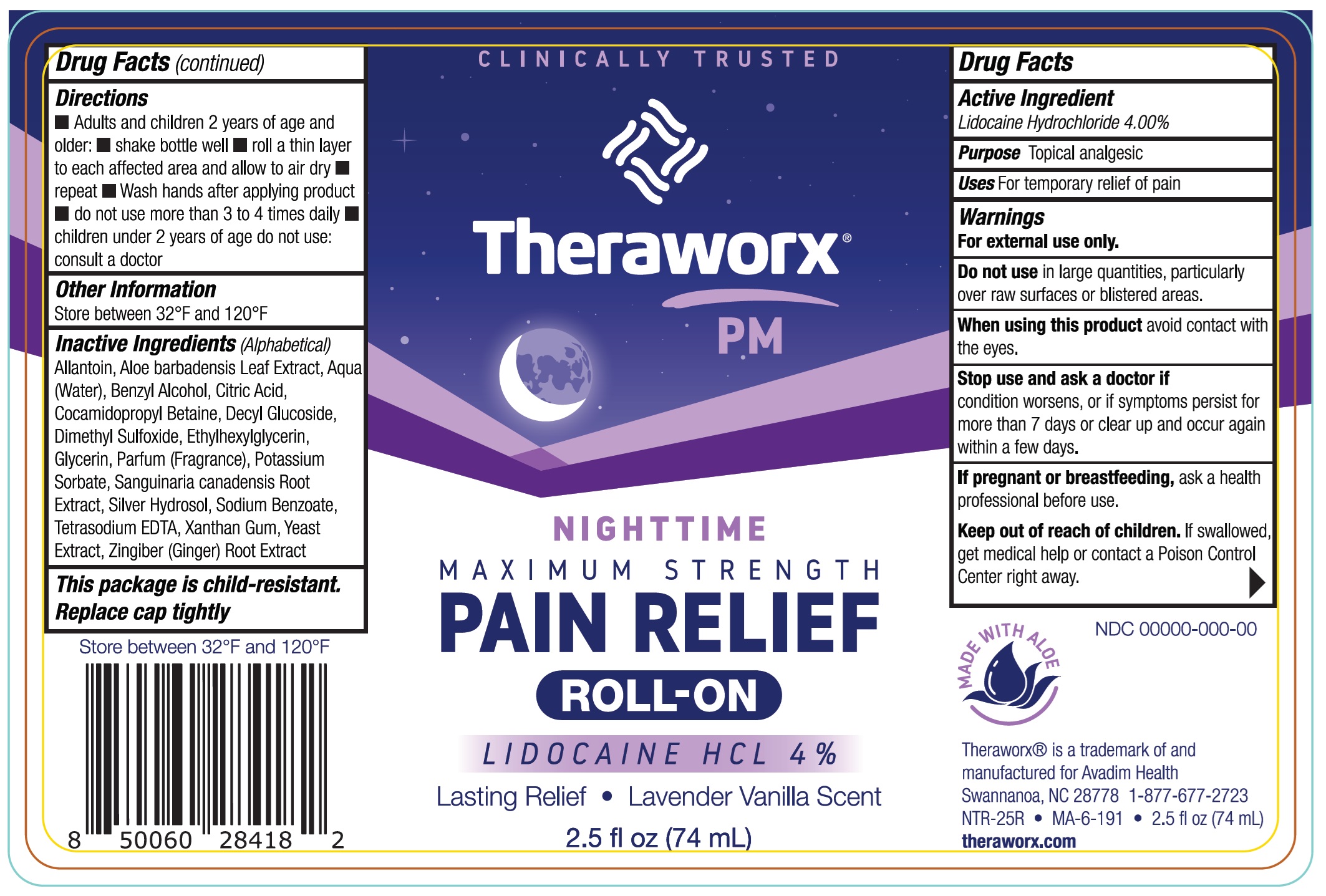 DRUG LABEL: Theraworx PM Nighttime Maximum Strength Pain Relief
NDC: 61594-044 | Form: LIQUID
Manufacturer: AVADIM HOLDINGS, INC.
Category: otc | Type: HUMAN OTC DRUG LABEL
Date: 20240919

ACTIVE INGREDIENTS: LIDOCAINE HYDROCHLORIDE 40 mg/1 mL
INACTIVE INGREDIENTS: ALLANTOIN; ALOE VERA LEAF; WATER; BENZYL ALCOHOL; CITRIC ACID MONOHYDRATE; COCAMIDOPROPYL BETAINE; DECYL GLUCOSIDE; DIMETHYL SULFOXIDE; ETHYLHEXYLGLYCERIN; GLYCERIN; POTASSIUM SORBATE; SANGUINARIA CANADENSIS ROOT; SODIUM BENZOATE; EDETATE SODIUM; XANTHAN GUM; YEAST, UNSPECIFIED; GINGER

Theraworx PM Nighttime Maximum Strength Pain Relief Roll-On

Active Ingredient

Lidocaine Hydrochloride 4.00%

Purpose

Topical analgesic

Uses

For temporary relief of pain

Warnings

For external use only.

Do not use

in large quantities, particularly over raw surfaces or bilstered areas.

When using this product

avoid contact with the eyes.

Stop use and ask a doctor if

condition worsens, or if symptoms persist for more than 7 days or clear up and occur again within a few days.

If pregnant or breastfeeding,

ask a health professional before use.

Keep out of reach of children.

If swallowed, get medical help or contact a Poison Control Center right away.

Directions

- Adults and children 2 years of age and older:
- shake bottle well
- roll a thin layer to each affected area and allow to air dry
- repeat
- Wash hands after applying product
- do not use more than 3 to 4 times daily
- children under 2 years of age do not use: consult a doctor

Other Information

Store between 32°F and 120°F

Inactive Ingredients (Alphabetical)

Allantoin, Aloe barbadensis Leaf Extract, Aqua(Water), Benzyl Alcohol, Citric Acid, Cocamidopropyl Betaine, Decyl Glucoside, Dimethyl Sulfoxide, Ethylhexylglycerin, Glycerin, Parfum (Fragrance), Potassium Sorbate, Sanguinaria canadensis Root Extract, Silver Hydrosol, Sodium Benzoate, Tetrasodium EDTA, Xanthan Gum, Yeast Extract, Zingiber (Ginger) Root Extract